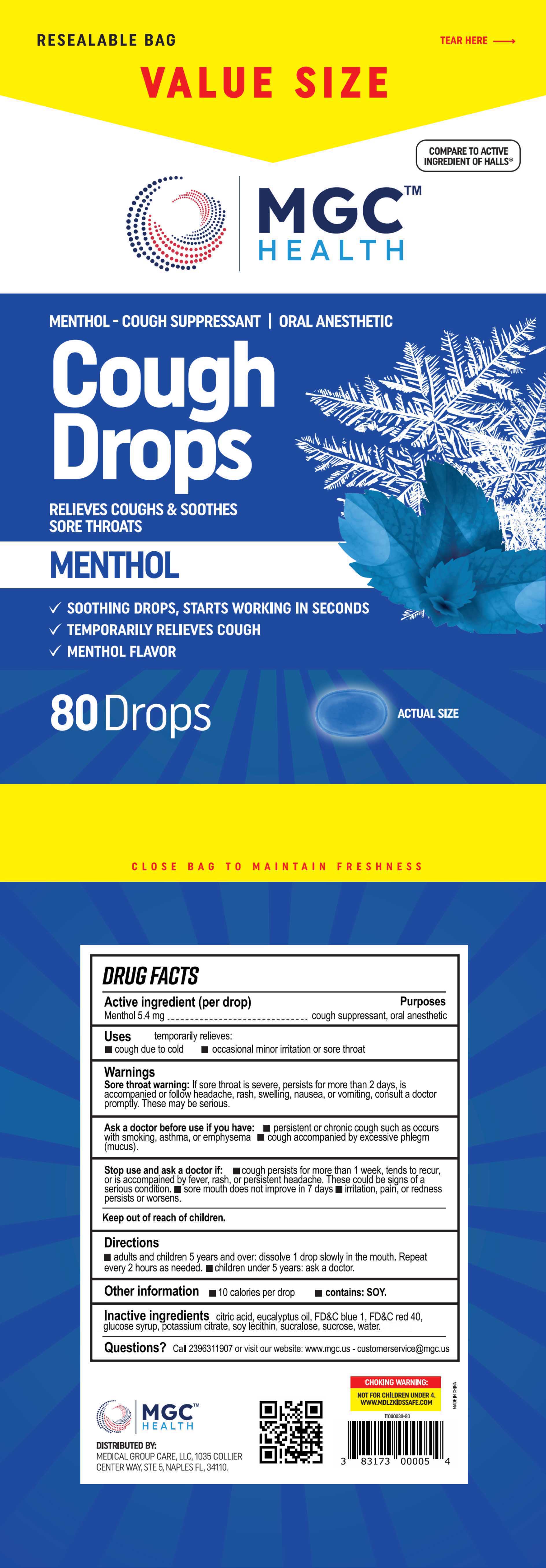 DRUG LABEL: Cough Drops
NDC: 80404-501 | Form: TABLET, ORALLY DISINTEGRATING
Manufacturer: Xinsanyang Pharmaceutical (Xiamen) Co., Ltd.
Category: otc | Type: HUMAN OTC DRUG LABEL
Date: 20231023

ACTIVE INGREDIENTS: MENTHOL 5.4 mg/1 1
INACTIVE INGREDIENTS: WATER; CITRIC ACID MONOHYDRATE; EUCALYPTUS OIL; FD&C BLUE NO. 1; CORN SYRUP; POTASSIUM CITRATE; LECITHIN, SOYBEAN; FD&C RED NO. 40; SUCRALOSE; SUCROSE

Cough Drops

Cough Drops

ACTIVE INGREDIENT

Menthol

PURPOSE

cough suppressant, oral anesthetic

INDICATIONS AND USAGE

temporarily relieves: cough due to cold, occasional minor irritation or sore throat

WARNINGS

Sore throat warning: lf sore throat is severe, persists for more than 2 days, isaccompanied or follow headache, rash, swelling, nausea, or vomiting, consult a doctorprompfly. These may be serious.

Ask a doctor before use if you have:persistent or chronic cough such as occurs with smoking, asthma, or emphysema

cough accompanied by excessive phlegm (mucus).

Stop use and ask a doctor if: cough persists for more than 1 week, tends to recur,
or is accompained by fever, rash, or persistent headache. These could be signs of a
serious condition. sore mouth does not improve in 7 days

irritation, pain, or redness persists or worsens.

WHEN USING

adults and children 5 years and over: dissolve 1 drop slowly in the mouth. Repeatevery 2 hours as needed.

children under 5 years: ask a doctor.

Stop use and ask a doctor if: cough persists for more than 1 week, tends to recur,
or is accompained by fever, rash, or persistent headache. These could be signs of a
serious condition. sore mouth does not improve in 7 days irritation, pain, or redness
persists or worsens.

Keep out of reach of children.

DOSAGE AND ADMINISTRATION

adults and children 5 years and over: dissolve 1 drop slowly in the mouth. Repeatevery 2 hours as needed.

children under 5 years: ask a doctor.

STORAGE AND HANDLING

Dry, avoid sunlight

INACTIVE INGREDIENT

EUCALYPTUS OIL
FD&C BLUE NO. 1
FD&C RED NO. 40
POTASSIUM CITRATE
SOY LECITHIN
SUCRALOSE
SUCROSE
GLUCOSE SYRUP
CITRIC ACID
Water